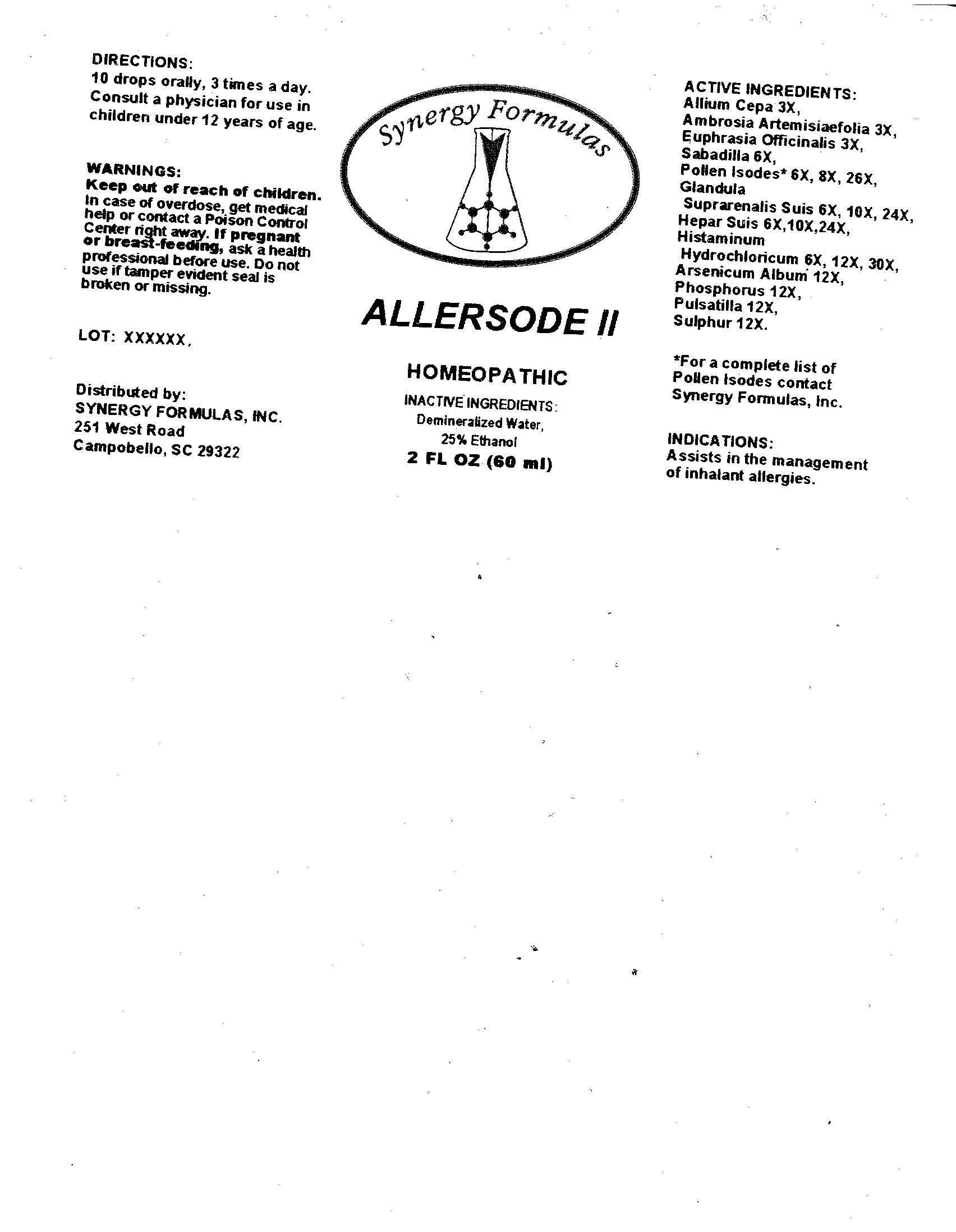 DRUG LABEL: Allersode
NDC: 57520-0522 | Form: LIQUID
Manufacturer: Apotheca Company
Category: homeopathic | Type: HUMAN OTC DRUG LABEL
Date: 20100729

ACTIVE INGREDIENTS: ONION 3 [hp_X]/1 mL; AMBROSIA ARTEMISIIFOLIA 3 [hp_X]/1 mL; EUPHRASIA STRICTA 3 [hp_X]/1 mL; SCHOENOCAULON OFFICINALE SEED 6 [hp_X]/1 mL; SUS SCROFA ADRENAL GLAND 24 [hp_X]/1 mL; PORK LIVER 24 [hp_X]/1 mL; HISTAMINE DIHYDROCHLORIDE 30 [hp_X]/1 mL; ARSENIC TRIOXIDE 12 [hp_X]/1 mL; PHOSPHORUS 12 [hp_X]/1 mL; PULSATILLA VULGARIS 12 [hp_X]/1 mL; SULFUR 12 [hp_X]/1 mL; PLATANUS OCCIDENTALIS POLLEN 26 [hp_X]/1 mL; FAGUS GRANDIFOLIA POLLEN 26 [hp_X]/1 mL; JUGLANS NIGRA POLLEN 26 [hp_X]/1 mL; SALIX NIGRA POLLEN 26 [hp_X]/1 mL; ACER NEGUNDO POLLEN 26 [hp_X]/1 mL; POPULUS DELTOIDES POLLEN 26 [hp_X]/1 mL; BETULA OCCIDENTALIS POLLEN 26 [hp_X]/1 mL; QUERCUS RUBRA POLLEN 26 [hp_X]/1 mL; CARYA OVATA POLLEN 26 [hp_X]/1 mL; POA PRATENSIS 26 [hp_X]/1 mL; DACTYLIS GLOMERATA 26 [hp_X]/1 mL; AGROSTIS GIGANTEA 26 [hp_X]/1 mL; PHLEUM PRATENSE 26 [hp_X]/1 mL; AMBROSIA ACANTHICARPA POLLEN 26 [hp_X]/1 mL; AMBROSIA TRIFIDA POLLEN 26 [hp_X]/1 mL; AMBROSIA PSILOSTACHYA POLLEN 26 [hp_X]/1 mL; AMBROSIA ARTEMISIIFOLIA POLLEN 26 [hp_X]/1 mL; RUMEX ACETOSELLA POLLEN 26 [hp_X]/1 mL; RUMEX CRISPUS POLLEN 26 [hp_X]/1 mL; FRAXINUS AMERICANA POLLEN 26 [hp_X]/1 mL; ULMUS AMERICANA POLLEN 26 [hp_X]/1 mL
INACTIVE INGREDIENTS: WATER; ALCOHOL

Allersode II

ACTIVE INGREDIENT

ACTIVE INGREDIENTS: Allium cepa3X, Ambrosia artemisiaefolia 3X, Euphrasia officinalis 3X, Sabadilla 6X, Glandula suprarenalis suis 6X, 10X, 24X, Hepar suis 6X, 10X, 24X, Histaminum hydrochloricum 6X, 12X, 30X, Arsenicum album 12X, Phosphorus 12X, Pulsatilla 12X, Sulphur 12X, (Tree Mixture) Ash 6X, 8X, 26X, American elm 6X, 8X, 26X, American sycamore 6X, 8X, 26X, Beech 6X, 8X, 26X, Black walnut 6X, 8X, 26X, Black willow 6X, 8X, 26X, Box elder 6X, 8X, 26X, Eastern cottonwood 6X, 8X, 26X, Red Birch 6X, 8X, 26X, Red oak 6X, 8X, 26X, Shagbark hickory 6X, 8X, 26X, (Grass Mixture) Kentucky bluegrass 6X, 8X, 26X, Orchard 6X, 8X, 26X, Redtop 6X, 8X, 26X, (Ragweed Mixture) Giant ragweed 6X, 8X, 26X, False ragweed 6X, 8X, 26X, Short ragweed 6X, 8X, 26X, Western ragweed 6X, 8X, 26X, (Sorrel Mixture) Sheep sorrel 6X, 8X, 26X, Yellow dock 6X, 8X, 26X.

PURPOSE

INDICATIONS: Assists in the management of inhalent allergies.

WARNINGS

WARNINGS: Keep out of reach of children. In case of overdose, get medical help or contact a Poison Control Center right away.

If pregnant or breast-feeding, ask a health professional before use.

Do not use if tamper evident seal is broken or missing.

DOSAGE AND ADMINISTRATION

DIRECTIONS: 10 drops orally, 3 times a day. Consult a physician for use in children under 12 years of age.

INACTIVE INGREDIENTS: Demineralized water, 25% Ethanol.

QUESTIONS

Distributed by:

SYNERGY FORMULAS, INC.

251 West Road

Campobello, SC 29322

For a complete list of Pollen Isodes contact Synergy Formulas, Inc.

PACKAGE LABEL

Synergy Formulas

ALLERSODE II

HOMEOPATHIC

2 FL OZ (60 ml)